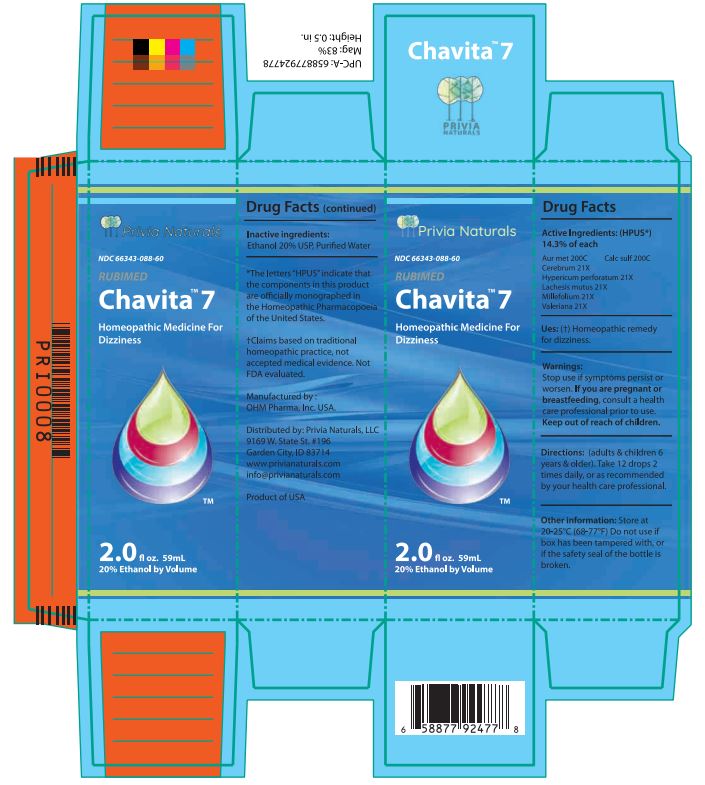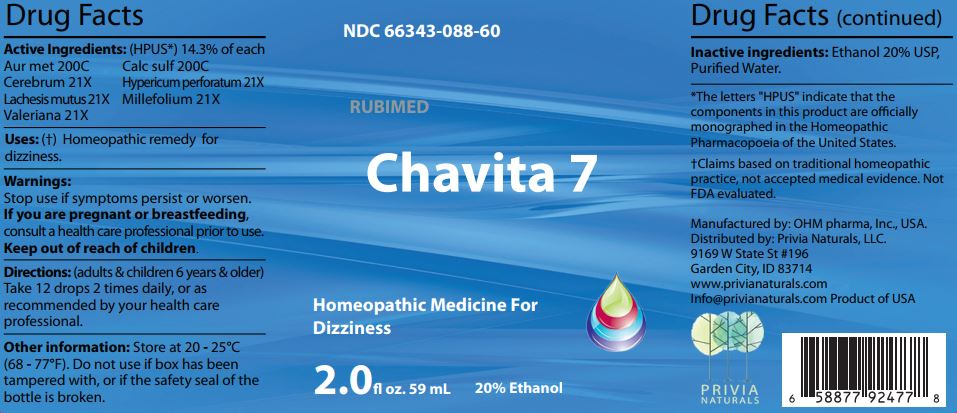 DRUG LABEL: Chavita 7
NDC: 66343-088 | Form: LIQUID
Manufacturer: RUBIMED AG
Category: homeopathic | Type: HUMAN OTC DRUG LABEL
Date: 20241029

ACTIVE INGREDIENTS: GOLD 200 [hp_C]/60 mL; CALCIUM SULFATE ANHYDROUS 200 [hp_C]/60 mL; SUS SCROFA CEREBRUM 21 [hp_X]/60 mL; HYPERICUM PERFORATUM WHOLE 21 [hp_X]/60 mL; LACHESIS MUTA VENOM 21 [hp_X]/60 mL; ACHILLEA MILLEFOLIUM WHOLE 21 [hp_X]/60 mL; VALERIAN 21 [hp_X]/60 mL
INACTIVE INGREDIENTS: ALCOHOL; WATER

Chavita 7

ACTIVE INGREDIENT

Drug Facts Active Ingredients: (HPUS*) 14.3% of each

Aur met 200C Calc sulf 200C
Cerebrum 21X Hypericum perforatum 21X
Lachesis mutus 21X Millefolium 21X
Valeriana 21X

*The letters "HPUS" indicate that the components in this product are officially monographed in the Homeopathic Pharmacopoeia of the United States. †Claims based on traditional homeopathic practice, not accepted medical evidence. Not FDA evaluated.

INDICATIONS AND USAGE

Uses: (†) Homeopathic remedy for dizziness.

Warnings:

Stop use if symptoms persist or worsen.

If you are pregnant or breastfeeding,consult a healthcare professional prior to use.

Keep out of reach of children.

DOSAGE AND ADMINISTRATION

Directions: (adults & children 6 years & older)

Take 12 drops 2 times daily, or as recommended by your health care professional.

Other information: Store at 20 - 25°C

(68 - 77°F.) Do not use if box has been

tampered with, or if the safety seal of the

bottle is broken.

Inactive ingredients:Ethanol 20% USP,

Purified Water.

QUESTIONS

Manufactured by: OHM pharma, Inc, USA.

Distributed by: Privia Naturals, LLC.

9169 W State St #196

Garden City, ID 83714

www.privianaturals.com

Info@privianaturals.com Product of USA.

PACKAGE LABEL

NDC 66343-088-60

RUBIMED

Chavita 7

Homeopathic Medicine For

Dizziness

2.0 fl oz. 59mL 20% Ethanol

PURPOSE

Homeopathic Medicine For

Dizziness